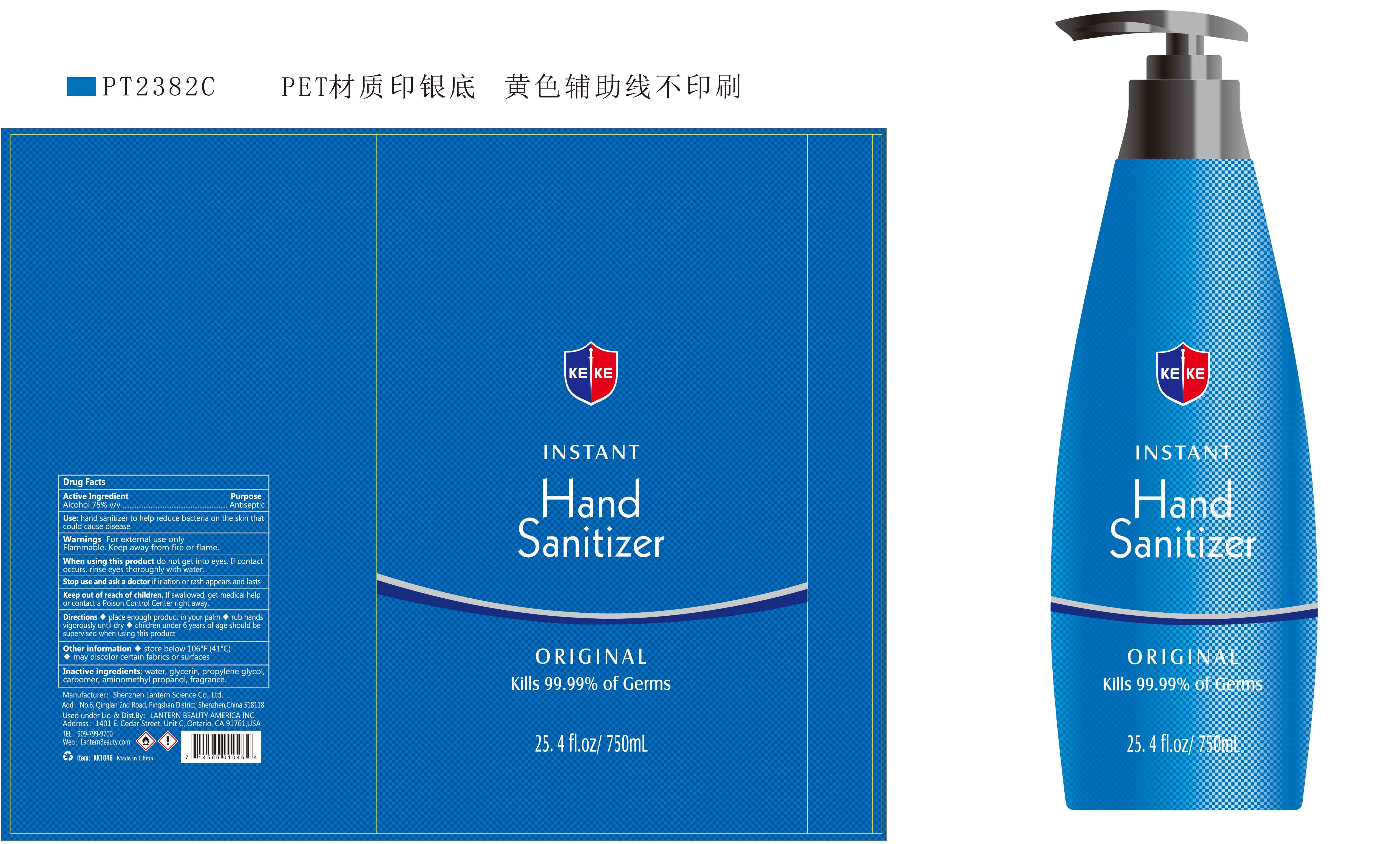 DRUG LABEL: KEKE hand sanitizer 750ml
NDC: 54860-372 | Form: LIQUID
Manufacturer: Shenzhen Lantern Scicence Co.,Ltd.
Category: otc | Type: HUMAN OTC DRUG LABEL
Date: 20210228

ACTIVE INGREDIENTS: ALCOHOL 75 mL/100 mL
INACTIVE INGREDIENTS: PROPYLENE GLYCOL 0.01 mL/100 mL; CARBOMER 940 0.35 mL/100 mL; AMINOMETHYLPROPANOL 0.11 mL/100 mL; WATER 24.42 mL/100 mL; GLYCERIN 0.01 mL/100 mL; LEMON 0.1 mL/100 mL

KEKE hand sanitizer 750ml

Active Ingredient

Active Ingredient Purpose

Ethyl Alcohol 75%（V/V） Antiseptic

Use

Hand sanitizer helps to reduce bacteria that potentially can cause disease.

Warning

For external use only,Flammable,Keep away from heat or flame.

WARNINGS AND PRECAUTIONS

For external use only.

Flammable, keep away from heat and flame.

STOP USE

Discontinue if skin becomes irritated and ask a doctor .

Keep out of reach of children. In case of accidental ingestion, seek professional assistance or contact a poson control center immediately.

When using this product

do not get into eyes,If contact occurs,rinse eyes thoroughly with water.

Stop use and ask a doctor

If iritation or rash appears and lasts.

keep out of reach of children

If swallowed,get medical help or contact a Poison Control Center right away.

DOSAGE AND ADMINISTRATION

Recommended for repeated use.

use anywhere without water.

Directions

place enough product in your palm

rub hands vigorously until dry

children under 6 years of age should be supervised when using this product.

When using this product

keep out of eyes. In case of contact with eyes, flush thoroughly with water.

Do not inhale or ingest.

Avoid contact with broken skin.

Other information

Do not store above 105F.

May discolor some fabrics.

Harmful to wood finishes and plastics.

Inactive ingredients

Water(Aqua),Glycerin,Propylene Glycol,,Carbomer,Aminomethyl propanolFragrance,

Other information

Store between 106℉（41℃).

May discolor certain fabrics or surfaces.

Purpose

Antiseptic